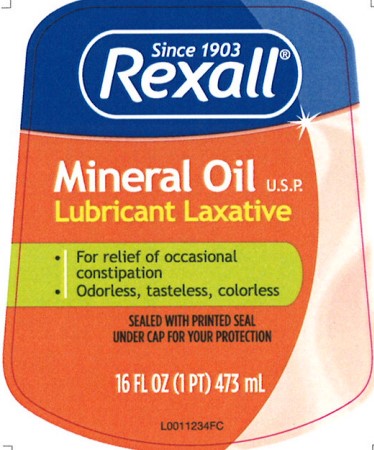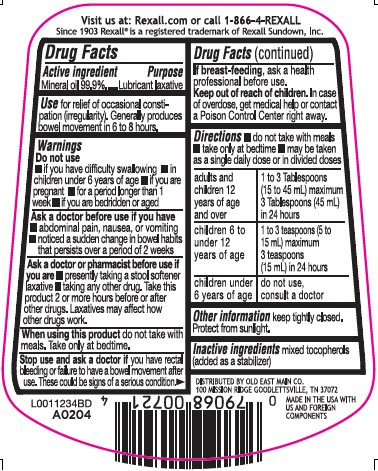 DRUG LABEL: Mineral Oil
NDC: 55910-831 | Form: LIQUID
Manufacturer: Old East Main Co.
Category: otc | Type: HUMAN OTC DRUG LABEL
Date: 20260302

ACTIVE INGREDIENTS: MINERAL OIL 999 mg/1 mL
INACTIVE INGREDIENTS: TOCOPHEROL

Rexall 831.000/831AA
Mineral Oil

Claims

Visit us at: Rexall.com or call 1-866-4-REXALL

Since 1903 Rexall is a registered trademark of Rexall Sundown, Inc.

Active ingredient

Mineral oil 99.9%

Purpose

Lubricant laxative

Use

for relief of occasional constipation (irregularity). Generally produces bowel movement in 6 to 8 hours.

Do not use

- if you have difficulty swallowing
- in children under 6 years of age
- if you are pregnant
- for a period longer than week
- if you are bedridden or aged

Ask a doctor before use if you have

- abdominal pain, nausea, or vomiting
- noticed a sudden change in bowel habits that persists over a period of 2 weeks

Ask a doctor or pharmacist before use if you are

- presently taking a stool softener laxative
- taking any other drug. Take this product 2 or more hours before or after other drugs. Laxatives may affect how other drugs work

When using this product

do not take with meals. Take only at bedtime.

Stop use and ask a doctor

if you have rectal bleeding or failure to have a bowel movement after use. These could be signs of a serious condition.

If breast-feeding,

ask a health professional before use.

Keep out of reach of children.

In case of overdose, get medical help or contact a Poison Control Center right away.

Directions

- do not take with meals
- take only at bedtime
- may be taken as a single daily dose or in divided doses

adults and children 12 years of age and over - 1 to 3 Tablespoons (15 to 45 mL) maximum 3 Tablespoons (45 mL) in 24 hours

children 6 to under 12 years of age - 1 to 3 teaspoons (5 to 15 mL) maximum 3 teaspoons (15 mL) in 24 hours

children under 6 years of age - do not use, consult a doctor

Other information

keep tightly closed. Protect from sunlight.

Inactive ingredients

mixed tocopherols (added as a stabilizer)

DISTRIBUTED BY OLD EAST MAIN CO

100 MISSION RIDGE GOODLETTSVILLE, TN 37072

MADE IN THE USA WITH US AND FOREIGN COMPONENTS

principal display panel

Since 1903

Rexall®

Mineral oil U.S.P.

Lubricant Laxative

- For relief of occasional constipation
- Odorless, tasteless, colorless

SEALED WITH PRINTED SEAL UNDER CAP FOR YOUR PROTECTION

16 FL OZ (1 PT) 473 mL